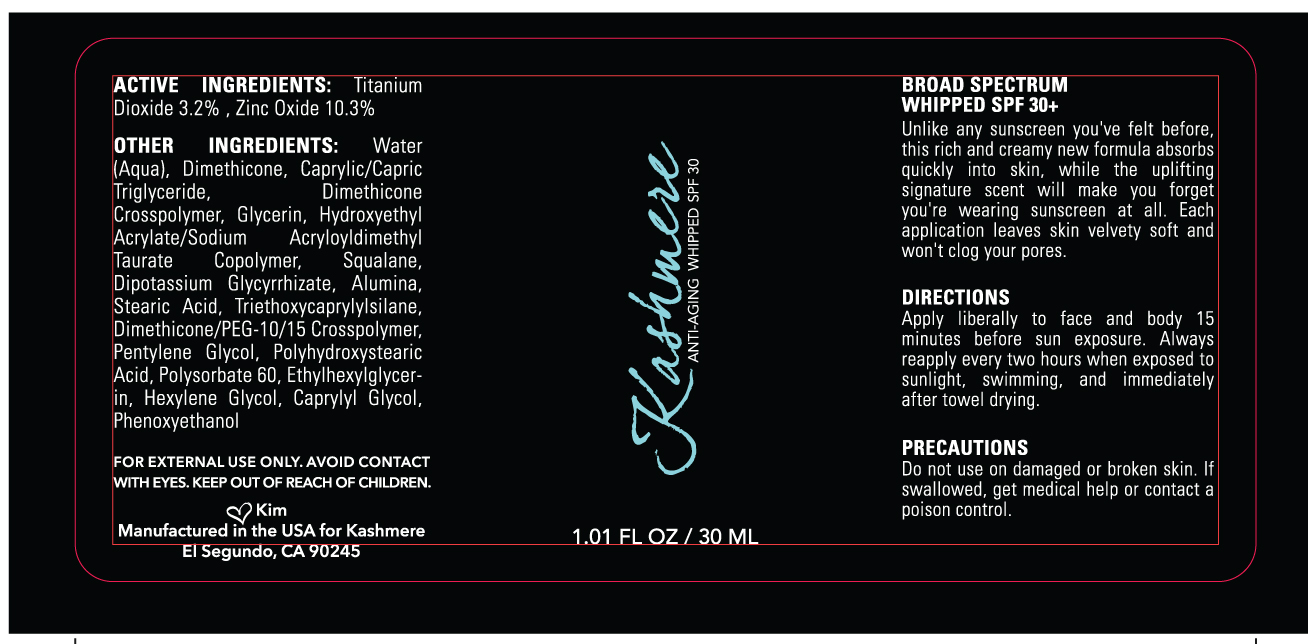 DRUG LABEL: Kashmere Anti-aging Sunscreen Moisturizer Broad Spectrum SPF 30
NDC: 72334-101 | Form: LOTION
Manufacturer: 323 Innovations
Category: otc | Type: HUMAN OTC DRUG LABEL
Date: 20180522

ACTIVE INGREDIENTS: TITANIUM DIOXIDE 3.2 g/100 mL; ZINC OXIDE 10.3 g/100 mL
INACTIVE INGREDIENTS: WATER; DIMETHICONE; MEDIUM-CHAIN TRIGLYCERIDES; DIMETHICONE CROSSPOLYMER (450000 MPA.S AT 12% IN CYCLOPENTASILOXANE); GLYCERIN; HYDROXYETHYL ACRYLATE/SODIUM ACRYLOYLDIMETHYL TAURATE COPOLYMER (45000 MPA.S AT 1%); SQUALANE; GLYCYRRHIZINATE DIPOTASSIUM; ALUMINUM OXIDE; STEARIC ACID; TRIETHOXYCAPRYLYLSILANE; PENTYLENE GLYCOL; POLYHYDROXYSTEARIC ACID (2300 MW); POLYSORBATE 60; ETHYLHEXYLGLYCERIN; HEXYLENE GLYCOL; CAPRYLYL GLYCOL; PHENOXYETHANOL

Kashmere Anti-aging Sunscreen Moisturizer Broad Spectrum SPF 30

Active Ingredients Purpose

Titanium Dioxide 3.2% Sunscreen

Zinc Oxide 10.3% Sunscreen

Uses
helps prevent sunburn
If used as directed with other sun protection measures (see Directions),
decreases the risk of skin cancer and early skin aging caused by the sun

Keep out of reach of children. If product is swallowed, get medical help or
contact a Poison Control Center right away.

Stop use and ask a doctor if rash occurs

Warnings

For external use only
Do not use on damaged or broken skin
When using this product keep out of eyes. Rinse with water to remove.

Directions
· Apply generously 15 minutes before sun exposure
· Reapply at least every 2 hours
· Use a water resistant sunscreen if swimming or sweating
· Children under 6 months: Ask a doctor
· Sun Protection Measures. Spending time in the sun increases your risk of skin
cancer and early skin aging. To decrease this risk, regularly use a sunscreen
with broad spectrum SPF of 15 or higher and other sun protection measures
including:
· limit time in the sun, especially from 10 a.m. - 2 p.m.
· wear long-sleeve shirts, pants, hats, and sunglasses

Inactive Ingredients

Water (Aqua), Dimethicone, Caprylic/Capric Triglyceride, Dimethicone Crosspolymer, Glycerin, Hydroxyethyl Acrylate/Sodium Acryloyldimethyl Taurate Copolymer, Squalane, Dipotassium Glycyrrhizate, Alumina, Stearic Acid, Triethoxycaprylylsilane, Dimethicone/PEG-10/15 Crosspolymer, Pentylene Glycol, Polyhydroxystearic Acid, Polysorbate 60, Ethylhexylglycerin, Hexylene Glycol, Caprylyl Glycol, Phenoxyethanol

PACKAGE LABEL

Kashmere

Anti-Aging Sunscreen Moisturizer

Whipped

Broad Spectrum SPF 30+

1 FL OZ / 30 ML